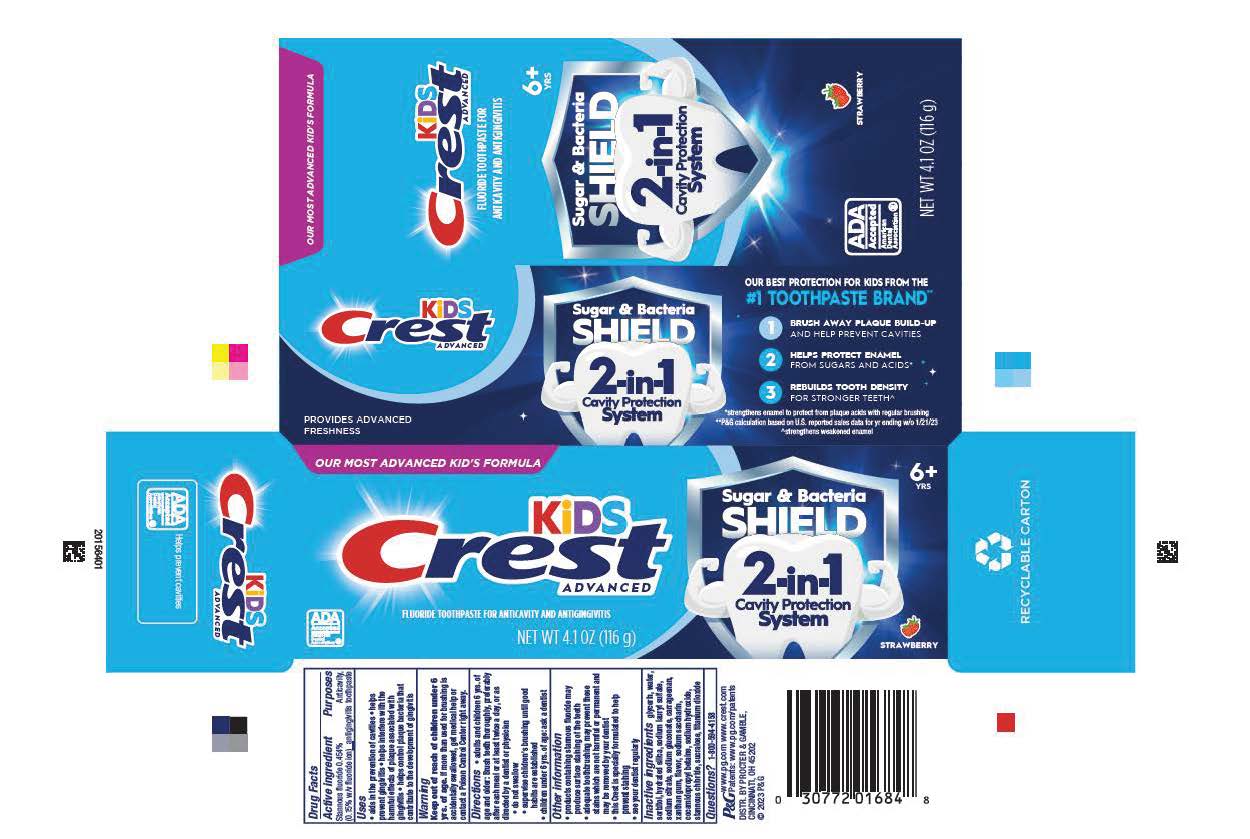 DRUG LABEL: KIDS Crest
NDC: 84126-612 | Form: PASTE, DENTIFRICE
Manufacturer: The Procter & Gamble Manufacturing Company
Category: otc | Type: HUMAN OTC DRUG LABEL
Date: 20250228

ACTIVE INGREDIENTS: STANNOUS FLUORIDE 1.5 mg/1 g
INACTIVE INGREDIENTS: GLYCERIN; COCAMIDOPROPYL BETAINE; STANNOUS CHLORIDE; WATER; HYDRATED SILICA; CARRAGEENAN; SODIUM GLUCONATE; XANTHAN GUM; SODIUM LAURYL SULFATE; SORBITOL; SODIUM HYDROXIDE; SUCRALOSE; TITANIUM DIOXIDE; SODIUM CITRATE; SACCHARIN SODIUM

Crest Kids Advanced Sugar & Bacteria Shield

Drug Facts

Active ingredient

Stannous fluoride 0.454%

(0.15% w/v fluoride ion)

Purposes

Anticavity, antigingivitis toothpaste

Use

• aids in the prevention of cavities • helps
prevent gingivitis • helps interfere with the
harmful effects of plaque associated with
gingivitis • helps control plaque bacteria that
contribute to the development of gingivitis

Warning

Keep out of reach of children under 6 yrs. of age. If more than used for brushing is accidentally swallowed, get medical help or contact a Poison Control Center right away.

Directions

• adults and children 6 yrs. of age and older: Brush teeth thoroughly, preferably after each meal or at least twice a day, or as directed by a dentist or physician.

• do not swallow

• supervise children's brushing until good habits are established

• children under 6 yrs. of age: ask a dentist

Other information

• products containing stannous fluoride may
produce surface staining of the teeth
• adequate toothbrushing may prevent these
stains which are not harmful or permanent and
may be removed by your dentist
• this Crest is specially formulated to help
prevent staining
• see your dentist regularly
Inactive ingredients

INACTIVE INGREDIENT

glycerin, water, sorbitol, hydrated silica, sodium lauryl sulfate, sodium citrate, sodium gluconate, carrageenan, xanthan gum, flavor, sodium saccharin, cocamidopropyl betaine, sodium hydroxide, stannous chloride, sucralose, titanium dioxide

Questions? 1-800-594-4158

DISTR. BY PROCTER & GAMBLE,

CINCINNATI, OH 45202

Crest Kids Advanced Sugar & Bacteria Shield

OUR MOST ADVANCED KID'S FORMULA

KID'S Crest® ADVANCED

FLUORIDE TOOTHPASTE FOR ANTICAVITY AND ANTIGINGIVITIS

ADA

ACCEPTED

AMERICAN

DENTAL

ASSOCIATION

NET WT 4.1 OZ (116 g)

6+ yrs

sugar & Bacteria

SHIELD

2-IN-1

Cavity Protection

System

STRAWBERRY